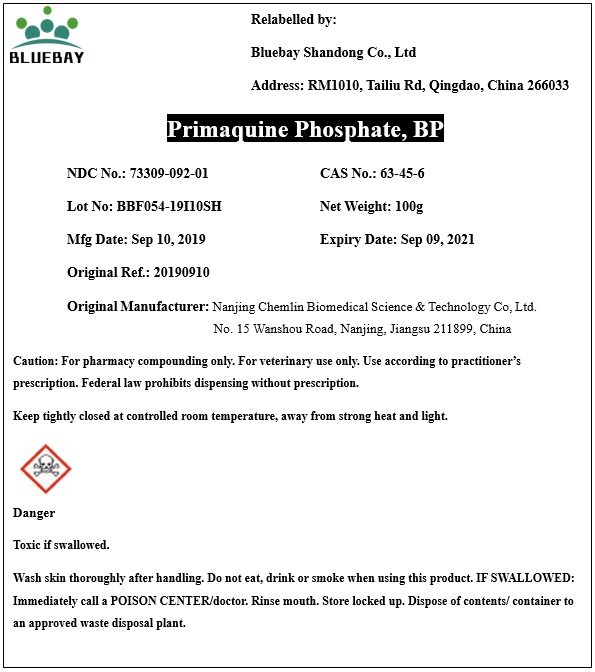 DRUG LABEL: Primaquine Phosphate
NDC: 73309-092 | Form: POWDER
Manufacturer: BLUEBAY SHANDONG CO.,LTD
Category: other | Type: BULK INGREDIENT
Date: 20200228

ACTIVE INGREDIENTS: PRIMAQUINE PHOSPHATE 1 g/1 g

Primaquine Phosphate